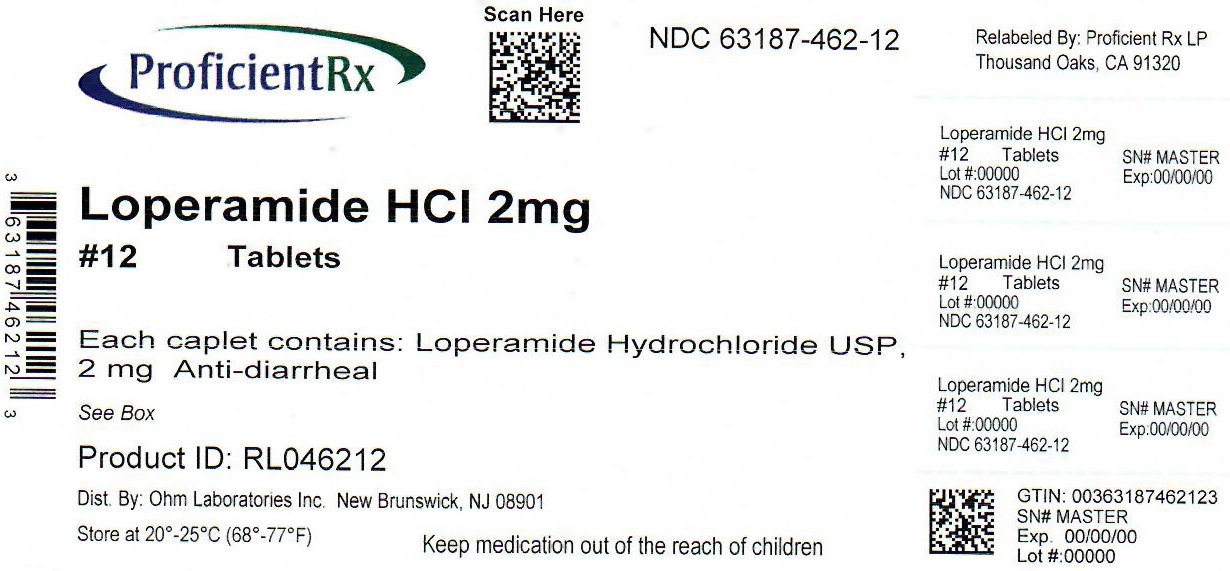 DRUG LABEL: Loperamide Hydrochloride
NDC: 63187-462 | Form: TABLET
Manufacturer: Proficient Rx LP
Category: otc | Type: HUMAN OTC DRUG LABEL
Date: 20220502

ACTIVE INGREDIENTS: LOPERAMIDE HYDROCHLORIDE 2 mg/1 1
INACTIVE INGREDIENTS: CROSCARMELLOSE SODIUM; CROSPOVIDONE (120 .MU.M); D&C YELLOW NO. 10; FD&C BLUE NO. 1; MAGNESIUM STEARATE; POWDERED CELLULOSE; STARCH, CORN; GLYCERYL TRISTEARATE; ANHYDROUS LACTOSE

Drug Facts

ACTIVE INGREDIENT (IN EACH CAPLET)

Loperamide HCl USP, 2 mg

PURPOSE

Anti-diarrheal

USE(S)

controls symptoms of diarrhea, including Travelers’ Diarrhea

WARNINGS

Allergy alert: Do not use if you have ever had a rash or other allergic reaction to loperamide HCI

Do not use

if you have bloody or black stool

Ask a doctor before use if you have

- fever
- mucus in the stool
- a history of liver disease

Ask a doctor or pharmacist before use if you are

taking antibiotics

When using this product

- tiredness, drowsiness or dizziness may occur. Be careful when driving or operating machinery.

Stop use and ask a doctor if

- diarrhea lasts for more than 2 days
- symptoms get worse
- you get abdominal swelling or bulging. These may be signs of a serious condition.

If pregnant or breast-feeding,

ask a health professional before use.

Keep out of reach of children.

In case of overdose, get medical help or contact a Poison Control Center right away (1-800-222-1222).

DIRECTIONS

- drink plenty of clear fluids to help prevent dehydration caused by diarrhea
- find right dose on chart. If possible, use weight to dose; otherwise, use age.

adults and children 12 years and over | 2 caplets after the first loose stool; 1 caplet after each subsequent loose stool; but no more than 4 caplets in 24 hours
children 9-11 years (60-95 lbs) | 1 caplet after the first loose stool; ½ caplet after each subsequent loose stool; but no more than 3 caplets in 24 hours
children 6-8 years (48-59 lbs) | 1 caplet after the first loose stool; ½ caplet after each subsequent loose stool; but no more than 2 caplets in 24 hours
children under 6 years (up to 47 lbs) | ask a doctor

OTHER INFORMATION

- store between 20° – 25° C (68° – 77° F)
- see side panel for lot number and expiration date
- TAMPER EVIDENT: THIS PRODUCT PROTECTED WITH SEALED BLISTER UNITS. DO NOT USE IF ANY ARE TORN OR BROKEN.

INACTIVE INGREDIENTS

anhydrous lactose, croscarmellose sodium, crospovidone, D&C yellow no.10, FD&C blue no.1, hydrogenated vegetable oil, magnesium stearate, powdered cellulose, pregelatinized starch

QUESTIONS?

call 1800-406-7984

Keep the carton. It contains important information.

Distributed by:

Ohm Laboratories Inc.

New Brunswick, NJ 08901

Relabeled by:

Proficient Rx LP

Thousand Oaks, CA 91320

PRINCIPAL DISPLAY PANEL

NDC 63187-462-12

Loperamide HCl Tablets, USP 2 mg

Anti-Diarrheal

12 CAPLETS†

Each caplet(† capsule-shaped tablet) contains Loperamide HCl, USP 2 mg

Controls The Symptoms of Diarrhea

* Compare to the active ingredient of Imodium® A-D

* This product is not manufactured or distributed by McNeil-PPC, distributor of Imodium® A-D.

Imodium® is a registered trademark of Johnson & Johnson.